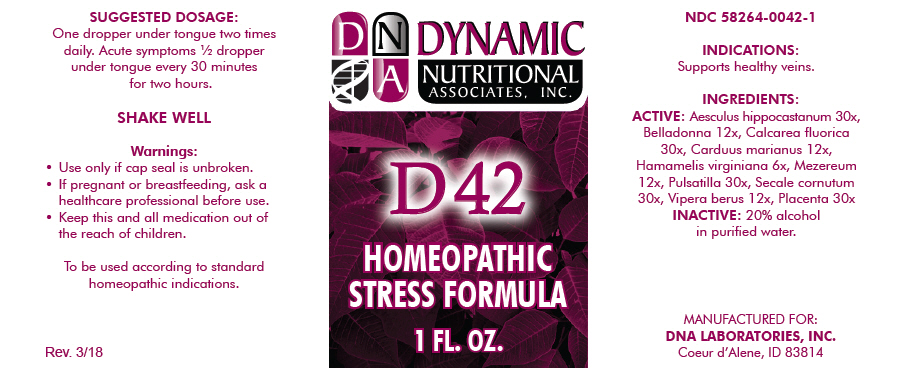 DRUG LABEL: D-42
NDC: 58264-0042 | Form: SOLUTION
Manufacturer: DNA Labs, Inc.
Category: homeopathic | Type: HUMAN OTC DRUG LABEL
Date: 20250113

ACTIVE INGREDIENTS: HORSE CHESTNUT 30 [hp_X]/1 mL; ATROPA BELLADONNA 12 [hp_X]/1 mL; CALCIUM FLUORIDE 30 [hp_X]/1 mL; MILK THISTLE 12 [hp_X]/1 mL; HAMAMELIS VIRGINIANA ROOT BARK/STEM BARK 6 [hp_X]/1 mL; DAPHNE MEZEREUM BARK 12 [hp_X]/1 mL; ANEMONE PRATENSIS 30 [hp_X]/1 mL; CLAVICEPS PURPUREA SCLEROTIUM 30 [hp_X]/1 mL; VIPERA BERUS VENOM 12 [hp_X]/1 mL; BOS TAURUS PLACENTA 30 [hp_X]/1 mL
INACTIVE INGREDIENTS: ALCOHOL; WATER

D-42

NDC 58264-0042-1

INDICATIONS

PURPOSE

Supports healthy veins.

INGREDIENTS

ACTIVE

Aesculus hippocastanum 30x, Belladonna 12x, Calcarea fluorica 30x, Carduus marianus 12x, Hamamelis virginiana 6x, Mezereum 12x, Pulsatilla 30x, Secale cornutum 30x, Vipera berus 12x, Placenta 30x

INACTIVE

20% alcohol in purified water.

SUGGESTED DOSAGE

One dropper under tongue two times daily. Acute symptoms ½ dropper under tongue every 30 minutes for two hours.

STORAGE AND HANDLING

SHAKE WELL

Warnings

- Use only if cap seal is unbroken.

PREGNANCY OR BREAST FEEDING

- If pregnant or breastfeeding, ask a healthcare professional before use.

KEEP OUT OF REACH OF CHILDREN

- Keep this and all medication out of the reach of children.

To be used according to standard homeopathic indications.

PRINCIPAL DISPLAY PANEL - 1 FL. OZ. Bottle Label

DYNAMIC
NUTRITIONAL
ASSOCIATES, INC.

D 42

HOMEOPATHIC
STRESS FORMULA

1 FL. OZ.